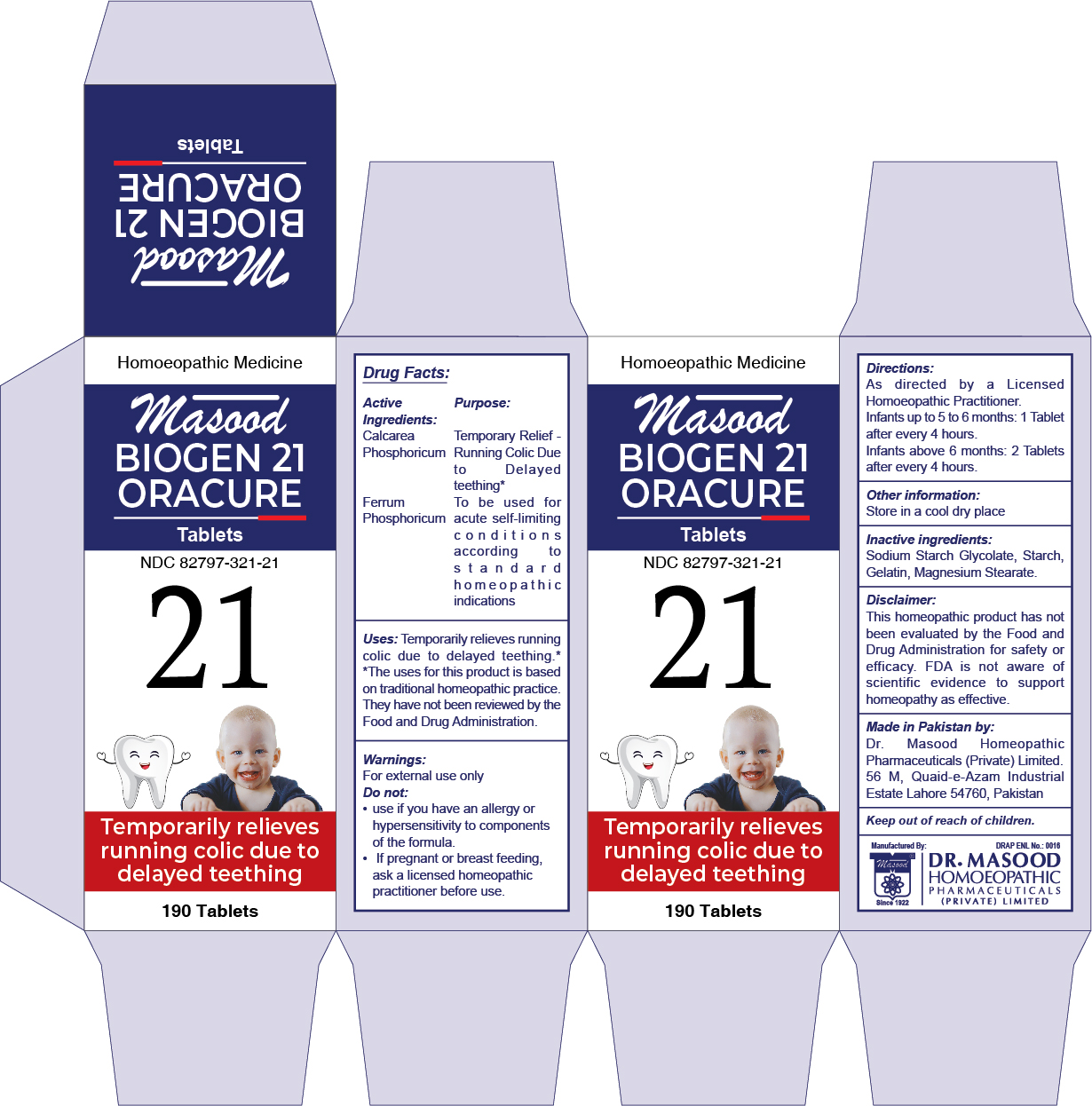 DRUG LABEL: Masood Biogen 21 Oracure
NDC: 82797-321 | Form: TABLET
Manufacturer: Dr. Masood Homeopathic Pharmaceuticals Private Limited
Category: homeopathic | Type: HUMAN OTC DRUG LABEL
Date: 20240109

ACTIVE INGREDIENTS: FERROSOFERRIC PHOSPHATE 48 mg/1 1; TRIBASIC CALCIUM PHOSPHATE 48 mg/1 1
INACTIVE INGREDIENTS: MAGNESIUM STEARATE 1.2 mg/1 1; SODIUM STARCH GLYCOLATE TYPE A CORN 0.76 mg/1 1; HYDROXYPROPYL CORN STARCH (5% SUBSTITUTION BY WEIGHT) 2.6 mg/1 1; GELATIN 0.2 mg/1 1

Masood Biogen 21 Oracure

Directions:

As directed by a Licensed Homoeopathic Practitioner.

- Infants up to 5 to 6 months: 1 Tablet after every 4 hours.
- Infants above 6 months: 2 Tablets after every 4 hours.

Uses:

Temporarily relieves running colic due to delayed teething. *

*The uses for this product is based on traditional homeopathic practice. They have not been reviewed by the Food and Drug Administration.

Active Ingredients

- Calcarea Phosphoricum
- Ferrum Phosphoricum

Keep out of reach of children.

Purpose

- Temporary Relief - Running Colic Due to Delayed teething*
- To be used for acute self-limiting conditions according to standard homeopathic indications

Inactive ingredients

Sodium Starch Glycolate, Starch, Gelatin, Magnesium Stearate

Warnings:

Do not:

- use if you have an allergy or hypersensitivity to components of the formula
- If pregnant or breast feeding, ask a licensed homeopathic practitioner before use